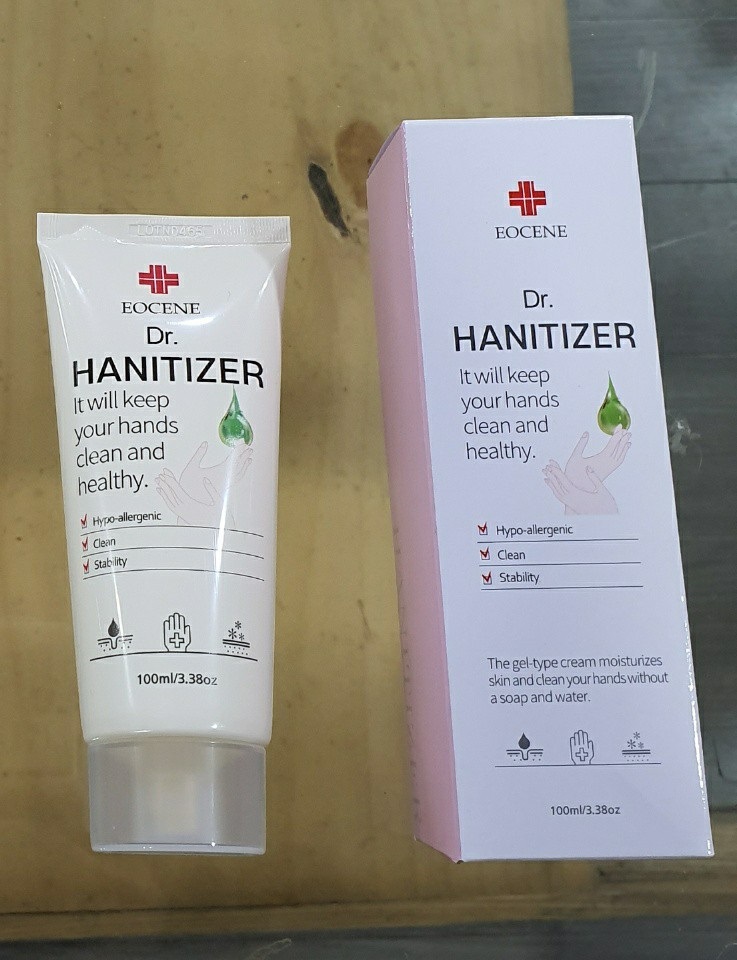 DRUG LABEL: EOCENE Dr. HANITIZER
NDC: 73466-0006 | Form: GEL
Manufacturer: MISOCOS
Category: otc | Type: HUMAN OTC DRUG LABEL
Date: 20240705

ACTIVE INGREDIENTS: ALCOHOL 62 mL/100 mL
INACTIVE INGREDIENTS: TROLAMINE; WATER; CARBOMER 940; ALOE VERA LEAF

Drug Facts

ACTIVE INGREDIENT

ethyl alcohol

PURPOSE

to decrease bacteria on the skin that could cause disease

recommended for repeated use

KEEP OUT OF REACH OF THE CHILDREN

WARNINGS

■ Flammable. Keep away from fire or flame.

■ For external use only.

■ Do not use in eyes.

■ lf swallowed, get medical help promptly.

■ Stop use, ask doctor lf irritation occurs.

■ Keep out of reach of children.

DOSAGE AND ADMINISTRATION

for external use only

INACTIVE INGREDIENT

Water
Carbomer
Triethanolamine
Fragrance
Camellia Sinensis Leaf Extract,
Aloe Barbadensis Leaf Extract

INDICATIONS AND USAGE

wet hands thoroughly with product and allow to dry without wiping

for children under 6, use only under adult supervision

not recommended for infants